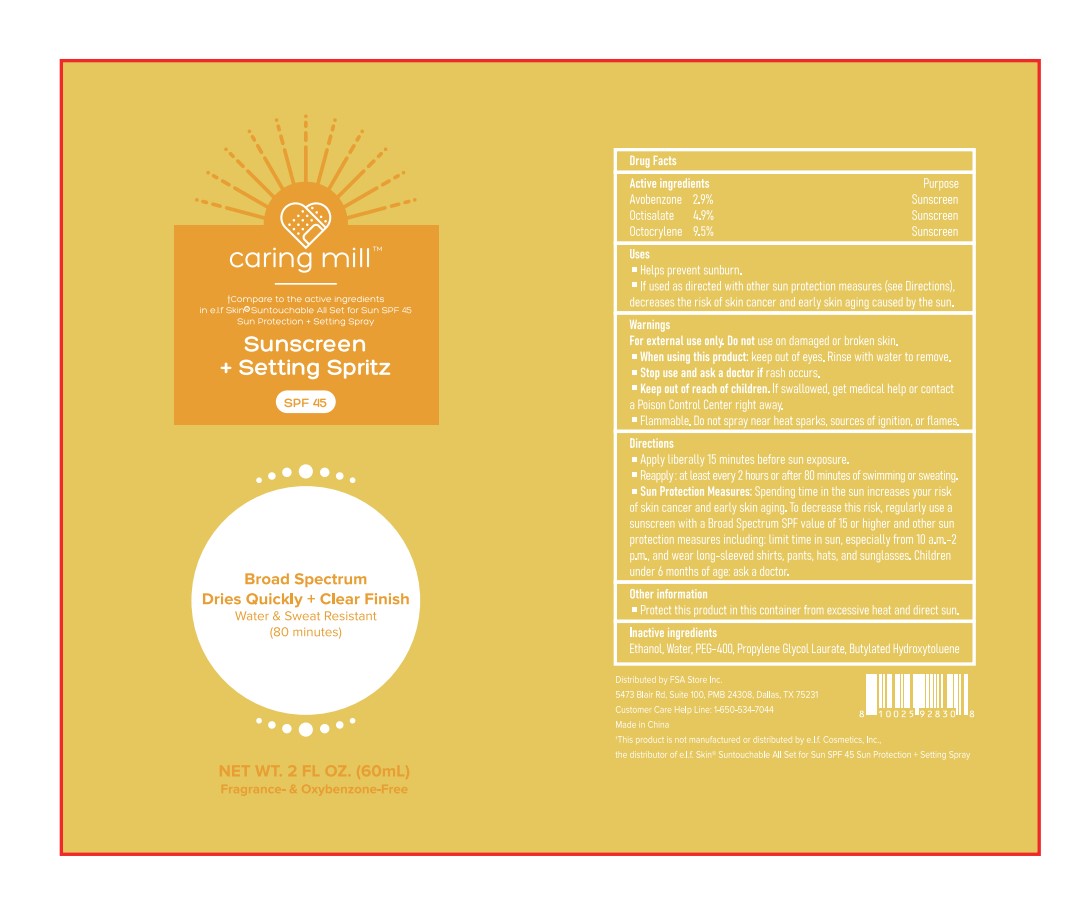 DRUG LABEL: SUNSCREEN SETTING SPRITZ, SPF 45
NDC: 87283-005 | Form: SPRAY
Manufacturer: Aopline Biotechnology (Guangzhou) Co., Ltd.
Category: otc | Type: HUMAN OTC DRUG LABEL
Date: 20260108

ACTIVE INGREDIENTS: OCTOCRYLENE 5.7 g/60 mL; OCTISALATE 2.94 g/60 mL; AVOBENZONE 1.74 g/60 mL
INACTIVE INGREDIENTS: PROPYLENE GLYCOL MONOLAURATE; WATER; ALCOHOL; BHT; POLYETHYLENE GLYCOL 400

87283-005-01 Sunscreen Setting Spritz, SPF 45

ACTIVE INGREDIENT

AVOBENZONE G63QQF2NOX 2.9%
OCTISALATE 4X49Y0596W 4.9%
OCTOCRYLENE 5A68WGF6WM 9.5%

PURPOSE

Sunscreen+ Setting Spritz

Keep out of reach of children.lf swallowed, get medical help or contacta Poison Control Center right away

INDICATIONS AND USAGE

Sun Protection Measures, Spending time in the sun increases your riskof skan cancer and early skin aging. lo decrease this risk, regularly use asunscreen with a Broad Spectrum SPF value of 15 or higher and other sunprotection measures including, limit time in sun, especiallv from 10 a.m.-2p.m, and wear long-sleeved shirts, pants, hats, and sunalasses. Chitdrenunder 6 months of age: ask a doctor.

DOSAGE AND ADMINISTRATION

Apply liberally 15 minutes before sun exposure. Reaooly. at least every 2 hours or after 80 minutes ofswimming or sweating.

INACTIVE INGREDIENT

WATER
BHT
ALCOHOL
PEG-400
PROPYLENE GLYCOL LAURATE

Warnings
For external use only Do not use on damaged or broken skin.
When using this product: keep out of eyes, Rinse with water to remove.
Stop use and ask a doctor if rash occurs.
Keep out of reach of children.lf swallowed, get medical help or contacta Poison Control Center right away
Flammable. Do not spray near heat sparks, sources of ignition, or flames